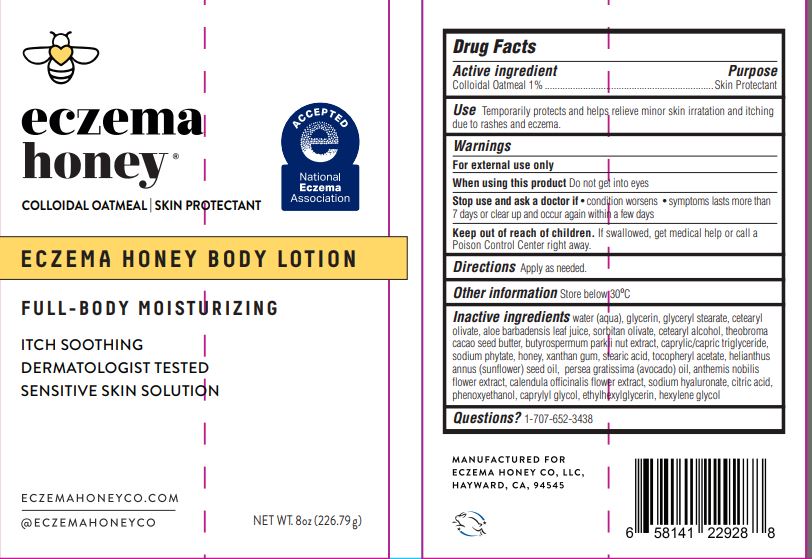 DRUG LABEL: EczemaHoneyBodyLotion
NDC: 62742-4234 | Form: LOTION
Manufacturer: Allure Labs
Category: otc | Type: HUMAN OTC DRUG LABEL
Date: 20231118

ACTIVE INGREDIENTS: OATMEAL 1 g/100 g
INACTIVE INGREDIENTS: GLYCERIN; CETEARYL OLIVATE; SHEANUT OIL; STEARIC ACID; SUNFLOWER OIL; AVOCADO OIL; HYALURONATE SODIUM; PHENOXYETHANOL; CAPRYLYL GLYCOL; HEXYLENE GLYCOL; CHAMAEMELUM NOBILE FLOWER; CALENDULA OFFICINALIS FLOWER; WATER; SORBITAN OLIVATE; CETOSTEARYL ALCOHOL; HONEY; XANTHAN GUM; .ALPHA.-TOCOPHEROL ACETATE; CITRIC ACID MONOHYDRATE; ETHYLHEXYLGLYCERIN; GLYCERYL MONOSTEARATE; ALOE VERA LEAF; COCOA BUTTER; MEDIUM-CHAIN TRIGLYCERIDES; PHYTATE SODIUM

Drug Facts

Active ingredient

Colloidal Oatmeal 1%

Purpose - Skin Protectant

INDICATIONS AND USAGE

Use Temporarily protects and helps relieve minor skin irritation and itching due to rashes and eczema

WARNINGS

For external use only

Do not use if condition worsens.

When using this product Do not get into eyes

Stop use and ask a doctor if • condition worsens • symptoms lasts more than 7 days or clear up and occur again within a few days

Keep out of reach of children. If swallowed, get medical help or call a Poison Control Center right away.

DOSAGE AND ADMINISTRATION

Directions Apply as needed.

Other information Store below 30°C

Inactive ingredients

water (aqua), glycerin, glyceryl stearate, cetearyl olivate, aloe barbadensis leaf juice, soritan olivate, cetearyl alcohol, theobroma cacao seed butter, butyrospermum parkii nut extract, caprylic/capric triglyceride, sodium phytate, honey, xanthan gum, stearic acid, tocopheryl acetate, helianthus annus (sunflower) seed oil, persea gratissima (avocado) oil, anthemis nobilis flower extract, calendula officinalis flower extract, sodium hyaluronate, citric acid, phenoxyethanol, caprylyl glycol, ethylhexylglycerin, hexylene glycol